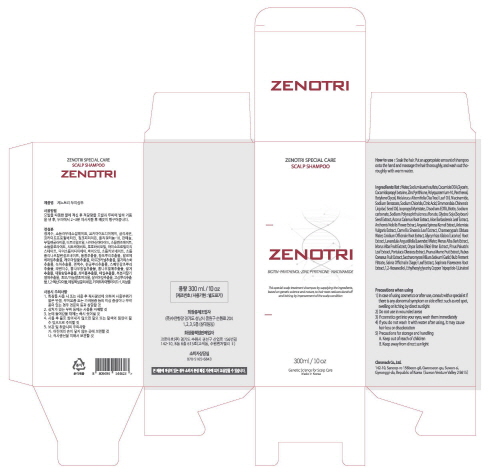 DRUG LABEL: ZENOTRI Scalp Shampoo.
NDC: 81817-301 | Form: SHAMPOO
Manufacturer: CHROMACH Co., Ltd.
Category: otc | Type: HUMAN OTC DRUG LABEL
Date: 20210513

ACTIVE INGREDIENTS: PYRITHIONE ZINC 2.98 g/300 mL
INACTIVE INGREDIENTS: COCO DIETHANOLAMIDE 9 mL/300 mL; COCAMIDOPROPYL BETAINE 9 mL/300 mL; GLYCERIN 6 mL/300 mL; PANTHENOL 1.5 mL/300 mL; SODIUM CHLORIDE 1.5 mL/300 mL; CHAMAEMELUM NOBILE FLOWER 0.01 mL/300 mL; PRUNUS MUME FRUIT 0.01 mL/300 mL; RUBUS COREANUS FRUIT 0.01 mL/300 mL; SOPHORA FLAVESCENS ROOT 0.01 mL/300 mL; 1,2-HEXANEDIOL 0.01 mL/300 mL; PREZATIDE COPPER 0.0003 mL/300 mL; CNIDIUM OFFICINALE ROOT 0.01 mL/300 mL; BIOTIN 0.18 mL/300 mL; SODIUM CARBONATE 0.12 mL/300 mL; FORMALDEHYDE/SODIUM NAPHTHALENESULFONATE COPOLYMER (3000 MW) 0.09 mL/300 mL; SOYBEAN 0.03 mL/300 mL; ALOE VERA LEAF 0.01 mL/300 mL; ACORUS CALAMUS ROOT 0.01 mL/300 mL; MORUS ALBA ROOT 0.01 mL/300 mL; RICE BRAN OIL 0.01 mL/300 mL; CHAMAECYPARIS OBTUSA WOOD OIL 0.01 mL/300 mL; GLYCYRRHIZA GLABRA 0.01 mL/300 mL; LAVENDER OIL 0.01 mL/300 mL; MORUS ALBA BARK 0.01 mL/300 mL; PINUS PALUSTRIS LEAF 0.01 mL/300 mL; SAGE 0.01 mL/300 mL; ETHYLHEXYLGLYCERIN 0.0006 mL/300 mL; WATER 225.7 mL/300 mL; SODIUM LAURETH SULFATE 36 mL/300 mL; TEA TREE OIL 1.17 mL/300 mL; NIACINAMIDE 0.9 mL/300 mL; EDETATE DISODIUM ANHYDROUS 0.3 mL/300 mL; SODIUM BENZOATE 0.3 mL/300 mL; JOJOBA OIL 1.5 mL/300 mL; GREEN TEA LEAF 0.01 mL/300 mL; GARLIC 0.01 mL/300 mL; POLYQUATERNIUM-10 (1000 MPA.S AT 2%) 2.26 mL/300 mL; PURSLANE 0.01 mL/300 mL; BUTYLENE GLYCOL 1.2 mL/300 mL; ISOPROPYL MYRISTATE 0.3 mL/300 mL; CITRIC ACID MONOHYDRATE 0.29 mL/300 mL; ARGAN OIL 0.01 mL/300 mL; ARTEMISIA VULGARIS ROOT 0.01 mL/300 mL

Active Ingredients

Pyrithione Zinc 1.05%

Purpose

Antidandruff

Use

For the relief of the symptoms of dandruff

Warnings

For external use only

When using this product avoid contact with the eyes. If contact occurs, rinse eyes thoroughly with water.

Stop use and ask a doctor if condition worsens or does not improve after regular use of this product as directed

Keep out of reach of children. If swallowed, get medical help or contact a Poison Control Center right away

Directions

For best results use at least twice a week or as directed by a doctor

Soak the hair. Put an appropriate amount of shampoo onto the hand and massage the hair thoroughly, and wash out thoroughly with warm water.

Inactive ingredients

Water, Sodium laureth sulfate, Cocamide DEA, Glycerin, Cocamidopropyl betaine, Zinc Pyrithione, Polyquaternium-10, Panthenol, Butylene Glycol, Melaleuca Alternifolia (Tea Tree) Leaf Oil, Niacinamide, Sodium Benzoate, Sodium Chloride, Citric Acid, Simmondsia Chinensis (Jojoba) Seed Oil, Isopropyl Myristate, Disodium EDTA, Biotin, Sodium carbonate, Sodium Polynaphthalenesulfonate, Glycine Soja (Soybean) Seed Extract, Acorus Calamus Root Extract, Aloe Barbadensis Leaf Extract, Anthemis Nobilis Flower Extract, Argania Spinosa Kernel Extract, Artemisia Vulgaris Extract, Camellia Sinensis Leaf Extract, Chamaecyparis Obtusa Water, Cnidium Officinale Root Extract, Glycyrrhiza Glabra (Licorice) Root Extract, Lavandula Angustifolia (Lavender) Water, Morus Alba Bark Extract, Morus Alba Fruit Extract, Oryza Sativa (Rice) Bran Extract, Pinus Palustris Leaf Extract, Portulaca Oleracea Extract, Prunus Mume Fruit Extract, Rubus Coreanus Fruit Extract, Saccharomyces/Allium Sativum (Garlic) Bulb Ferment Filtrate, Salvia Officinalis (Sage) Leaf Extract, Sophora Flavescens Root Extract, 1,2-Hexanediol, Ethylhexylglycerin, Copper Tripeptide-1